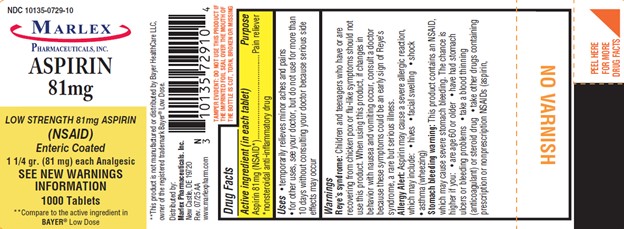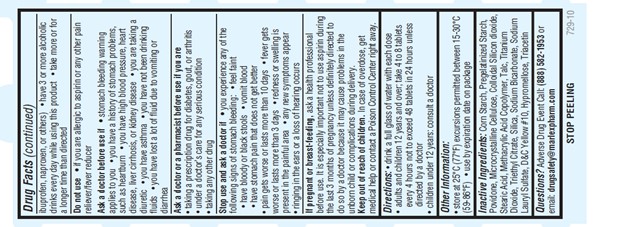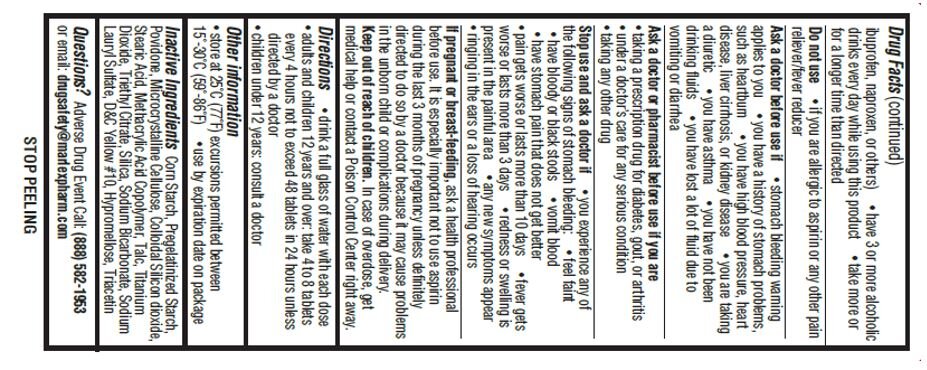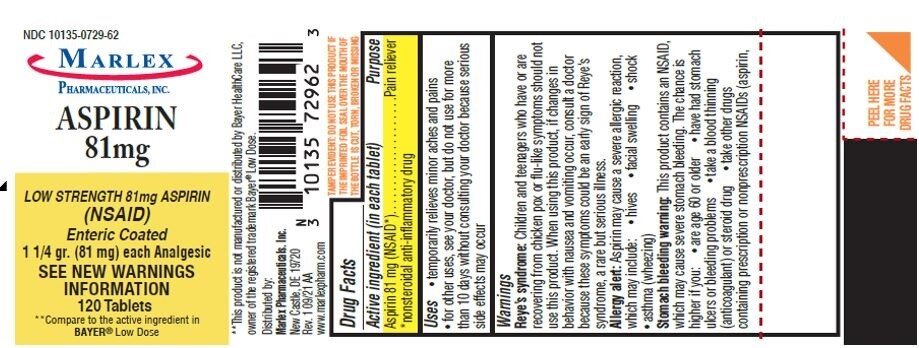 DRUG LABEL: Aspirin
NDC: 10135-729 | Form: TABLET
Manufacturer: Marlex Pharmaceuticals Inc.
Category: otc | Type: HUMAN OTC DRUG LABEL
Date: 20250805

ACTIVE INGREDIENTS: ASPIRIN 81 mg/1 1
INACTIVE INGREDIENTS: TITANIUM DIOXIDE; D&C YELLOW NO. 10; SODIUM BICARBONATE; SODIUM LAURYL SULFATE; STARCH, CORN; MICROCRYSTALLINE CELLULOSE; METHACRYLIC ACID - METHYL METHACRYLATE COPOLYMER (1:1); TRIETHYL CITRATE; SILICON DIOXIDE; TRIACETIN; POVIDONE, UNSPECIFIED; STEARIC ACID; HYPROMELLOSE, UNSPECIFIED; TALC

ASPIRIN 81MG TABLETS

Drug Fact

Active ingredient (in each tablet)

Aspirin 81mg (NSAID*)

*nonsteroidal anti-inflammatory drug

Purpose

Pain Reliever

Uses

· Temporarily relieves minor aches and pains.
· For other uses, see your doctor, but do not use for more than 10 days without consulting your doctor because serious side effects may occur

Warnings

Reye’s syndrome:Children and teenagers who have or are recovering from chicken pox or flu-like symptoms should not use this product. When using this product, if changes in behavior with nausea and vomiting occur, consult a doctor because these symptoms could be an early sign of Reye’s syndrome, a rare but serious illness.

Allergy Alert:Aspirin may cause a severe allergic reaction, which may include:
· Hives
· Facial Swelling
· Shock
· Asthma (wheezing)

Stomach bleeding warning:This product contains an NSAID, which may cause severe stomach bleeding. The chance is higher if you:
· Are age 60 or older
· Have had stomach ulcers or bleeding problems
· Take a blood thinning (anticoagulant) or steroid drug
· Take other drugs containing prescription or nonprescription NSAIDs (aspirin, ibuprofen, naproxen, or others)
· Have 3 or more alcoholic drinks every day while using this product
· Take more or for a longer time than directed

Do not useif you are allergic to aspirin or any other pain reliever/fever reducer

Ask a doctor before use if

· Stomach bleeding warning applies to you
· You have a history of stomach problems, such as heartburn
· You have high blood pressure, heart disease, liver cirrhosis, or kidney disease
· You are taking a diuretic
· You have asthma
· You have not been drinking fluids
· You have lost a lot of fluid due to vomiting or diarrhea

Ask a doctor or a pharmacist before use if you are

· Taking a prescription drug for diabetes, gout, or arthritis
· Under a doctor’s care for any serious condition
· Taking any other drug

Stop use and ask a doctor if

· You experience any of the following signs of stomach bleeding
· Feel faint
· Have bloody or black stools
· Vomit blood
· Have stomach pain that does not get better
· Pain gets worse or lasts more than 10 days
· Fever gets worse or lasts more than 3 days
· Redness or swelling is present in the painful area
· Any new symptoms appear
· Ringing in the ears or a loss of hearing occurs

If pregnant or breast-feeding,

ask a health professional before use. It is especially important not to use aspirin during the last 3 months of pregnancy unless definitely directed to do so by a doctor because it may cause problem in the unborn child or complications during delivery.

Keep out of reach of children.

In case of overdose, get medical help or contact a Poison Control Center right away.

Directions:

· Drink a full glass of water with each dose
· Adults and children 12 years and over; take 4 to 8 tablets every 4 hours not to exceed 48 tablets in 24 hours unless directed by a doctor
· Children under 12 years: consult a doctor

Other Information:

· Store at 25°C (77°F) excursions permitted between 15-30°C (59-86°F)
· Use by expiration date on package

Inactive Ingredients:

Corn Starch, Pregelatinized Starch, Povidone, Microcrystalline Cellulose, Stearic Acid, Colloidal Silicon Dioxide, Methacrylic Acid Co-Polymer, Triethyl Citrate, Talc, Titanium Dioxide, Silica, Sodium bicarbonate, Sodium lauryl sulfate, D&C Yellow #10, Hypromellose, Triacetin

Questions?

Adverse Drug Event Call: (888) 582 1953or Email: drugsafety@marlexpharm.com

PRINCIPAL DISPLAY PANEL

Distributed by:

Marlex Pharmaceuticals, Inc.

New Castle, DE 19720

www.marlexpharm.com

NDC 10135-0729-10

NDC 10135-0729-62